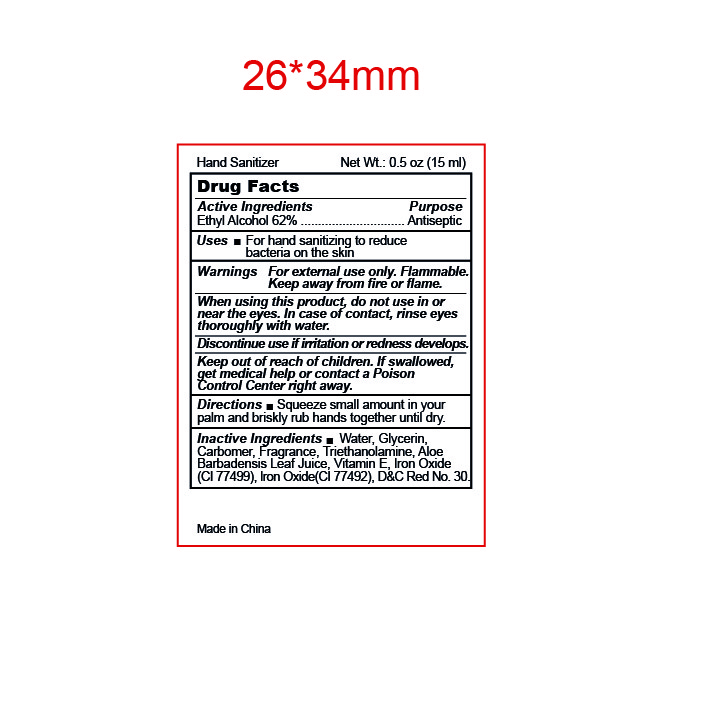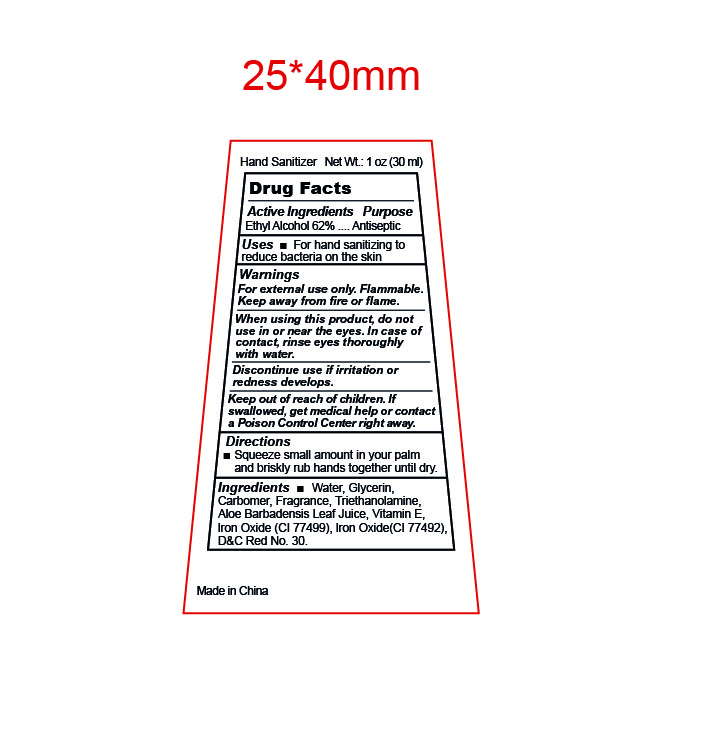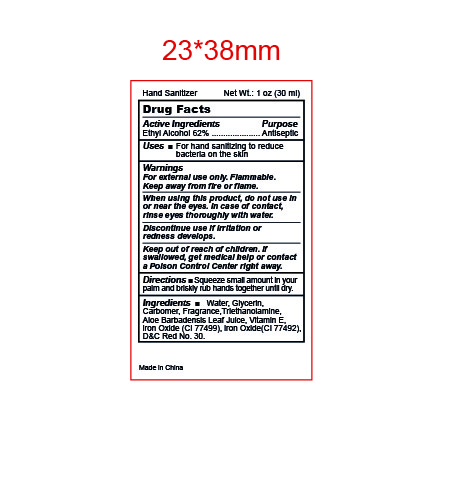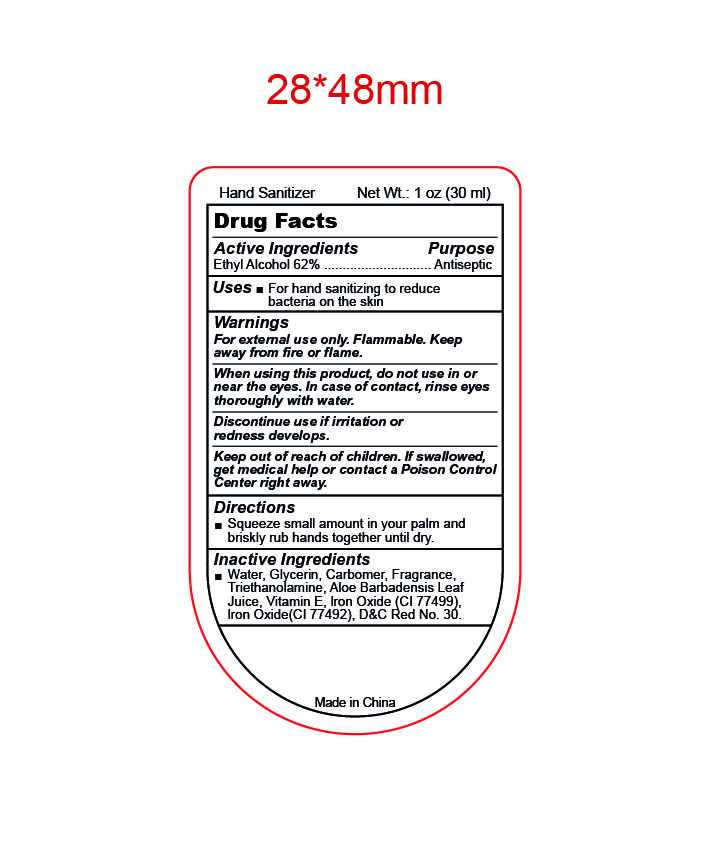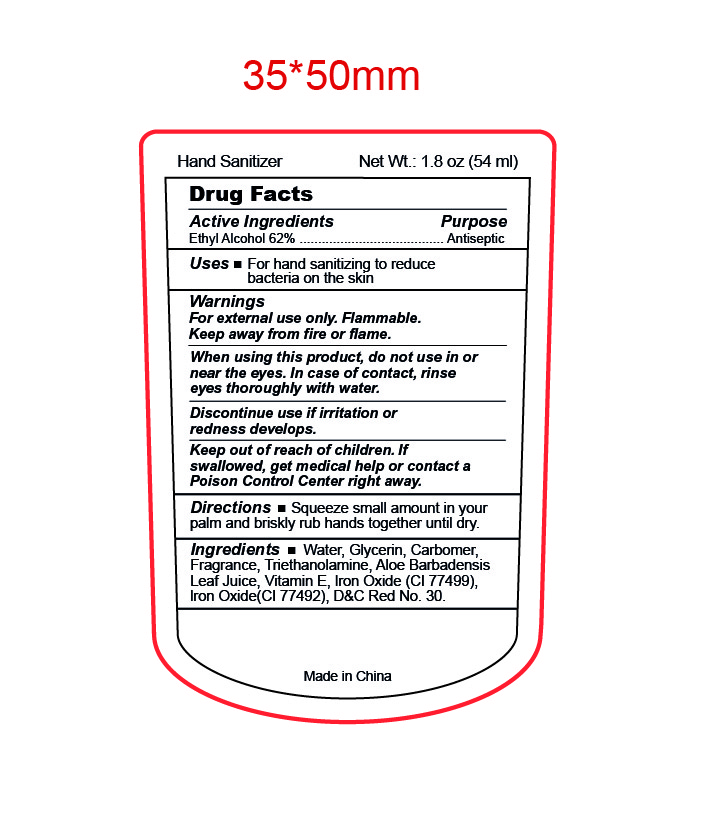 DRUG LABEL: Hand Sanitizer
NDC: 47993-363 | Form: GEL
Manufacturer: NINGBO JIANGBEI OCEAN STAR TRADING CO.,LTD
Category: otc | Type: HUMAN OTC DRUG LABEL
Date: 20250613

ACTIVE INGREDIENTS: ALCOHOL 62 g/112 mL
INACTIVE INGREDIENTS: WATER; GLYCERIN; CARBOMER INTERPOLYMER TYPE B (ALLYL PENTAERYTHRITOL CROSSLINKED); TROLAMINE; ALOE VERA LEAF; .ALPHA.-TOCOPHEROL; FERROSOFERRIC OXIDE; FERRIC OXIDE YELLOW; D&C RED NO. 30

47993-363

Active ingredients

Ethyl Alcohol 62%

PURPOSE

Antiseptic

Uses：

For hand sanitizing to reduce bacteria on the skin.

Warnings:

For external use only.

Flammable. Keep away from fire and flame.

When using this product，do not use in or near the eyes.In case of contact，rinse eyes thoroughly with water.

Discontinue use if irritation or redness develops.

Keep out of reach of children.If swallowed，get medical help or contact a Poison Control Center right away.

Directions:

Squeeze small amount in your palm and briskly rub hands together until dry.

Inactive Ingredients:

Water, Glycerin, Carbomer, Fragrance, Triethanolamine, Aloe Barbadensis Leaf Juice, Vitamin E, Iron Oxide（CI77499), Iron Oxide(CI 77492), D&C Red No.30.